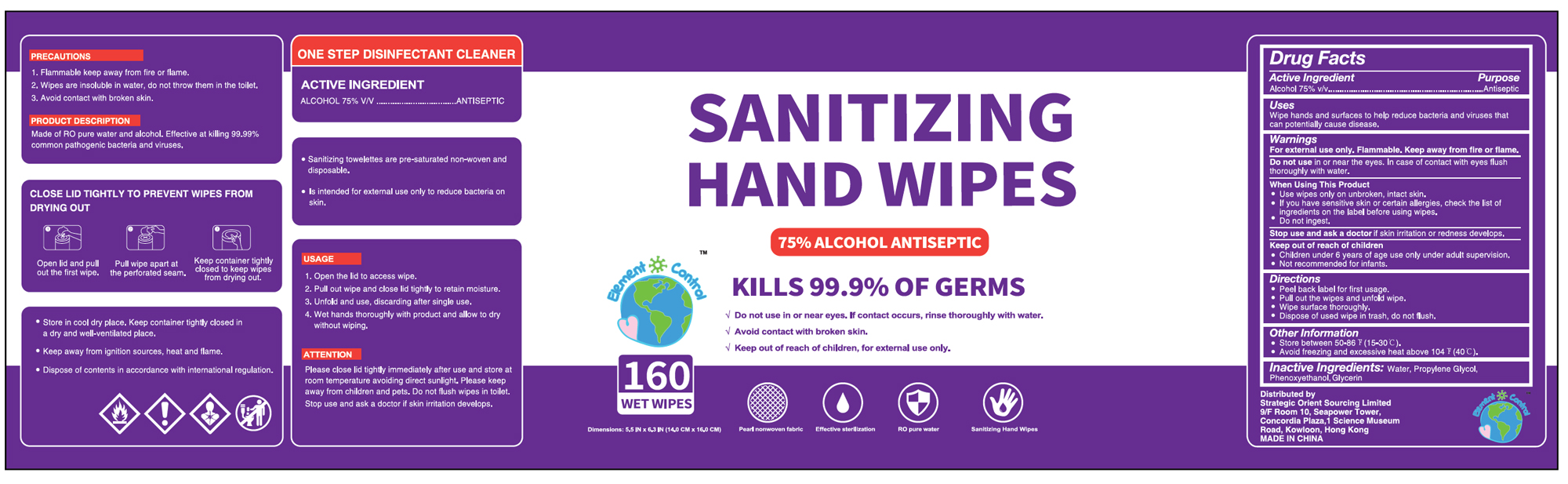 DRUG LABEL: sanitizing wipes
NDC: 79995-001 | Form: CLOTH
Manufacturer: Strategic Orient Sourcing Limited
Category: otc | Type: HUMAN OTC DRUG LABEL
Date: 20200730

ACTIVE INGREDIENTS: ALCOHOL 0.75 mL/1 g
INACTIVE INGREDIENTS: WATER; GLYCERIN; PHENOXYETHANOL; PROPYLENE GLYCOL

sanitizing wipes

ACTIVE INGREDIENT

Alcohol 75%. Purpose: Antiseptic

PURPOSE

Antiseptic

Uses

Wipe hands and surfaces to help reduce bacteria and viruses that can potenitally cause disease.

Warnings

- For external use only;
- Flammable; Keep away from fire or flame

Do not use

in or near the eyes. In case of contact with eyes flush thoroughly with water.

When using this product

- Use wipes only on unbroken, intact skin.
- If you have sensitive skin or certain allergies, check the list of ingredients on the label before using wipes.
- Do not ingest.

Stop use and ask a doctor

if skin irritation or redness develops

Keep out of reach of children

Children under 6 years of age use only under adult supervision

Not recommended for infants

Directions

Peel back label for first usage.

Pull out the wipes and unfold wipe.

Wipe surface thoroughly.

Dispose of used wipe in trash, do not flush

Other information

- Store between 50-86F (15-30C)
- Avoid freezing and excessive heat above 104F (40C)

Inactive Ingredients

Water, Propylene Glycol, phenoxyethanol, Glycerin

Package Label - Principal Display Panel

160 PCS NDC: 79995-001-01